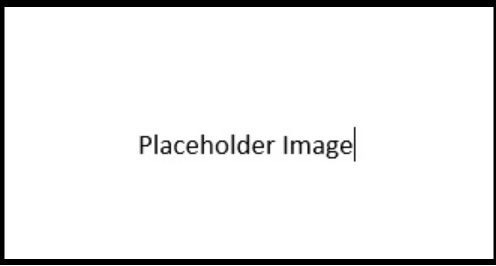 DRUG LABEL: Non-Drowsy Allergy Relief
NDC: 11673-621 | Form: TABLET
Manufacturer: TARGET CORPORATION
Category: otc | Type: HUMAN OTC DRUG LABEL
Date: 20250801

ACTIVE INGREDIENTS: Fexofenadine Hydrochloride 180 mg/1 1
INACTIVE INGREDIENTS: SILICON DIOXIDE; CROSCARMELLOSE SODIUM; magnesium stearate; mannitol; POWDERED CELLULOSE; FD&C RED NO. 40; HYPROMELLOSE 2910 (6 MPA.S); FERROSOFERRIC OXIDE; polyethylene glycol 400; TITANIUM DIOXIDE; STARCH, CORN

Fexofenadine HCl Tablets USP

Active ingredient (in each tablet)

Fexofenadine HCl USP, 180 mg

Purpose

Antihistamine

Uses

temporarily relieves these symptoms due to hay fever or other upper respiratory allergies:

- runny nose
- itchy, watery eyes
- sneezing
- itching of the nose or throat

Warnings

Do not use

if you have ever had an allergic reaction to this product or any of its ingredients.

Ask a doctor before use if you have

kidney disease. Your doctor should determine if you need a different dose.

When using this product

- do not take more than directed
- do not take at the same time as aluminum or magnesium antacids
- do not take with fruit juices (see Directions)

Stop use and ask doctor if

an allergic reaction to this product occurs. Seek medical help right away.

If pregnant or breast-feeding,

ask a health professional before use.

Keep out of reach of children.

In case of overdose, get medical help or contact a Poison Control Center right away.

Directions

adults and children 12 years of age and over | take one 180 mg tablet with water once a day; do not take more than 1 tablet in 24 hours
children under 12 years of age | do not use
adults 65 years of age and older | ask a doctor
consumers with kidney disease | ask a doctor

Other information

- safety sealed: do not use if carton is opened or if printed foil inner seal on bottle is torn or missing
- store between 20° and 25°C (68° and 77°F)
- protect from excessive moisture
- this product meets the requirements of USP Dissolution Test 4

Inactive ingredients

colloidal silicon dioxide, corn starch, croscarmellose sodium, FD&C Red no. 40, hypromellose, iron oxide black, magnesium stearate, mannitol, polyethylene glycol, powder cellulose and titantium dioxide

Questions?

call 1-888-375-3784

Carton Label

70ct Container and Container Carton labels